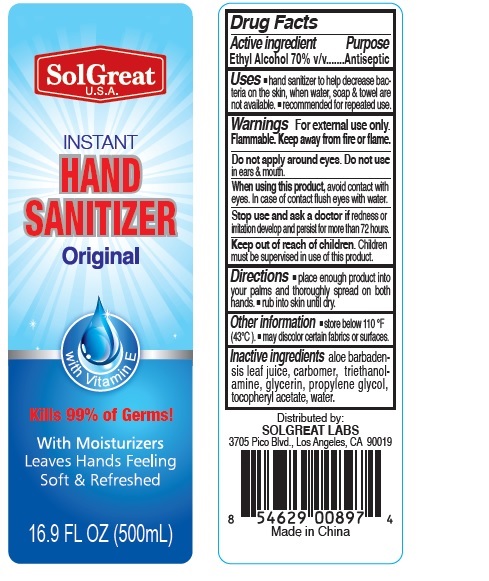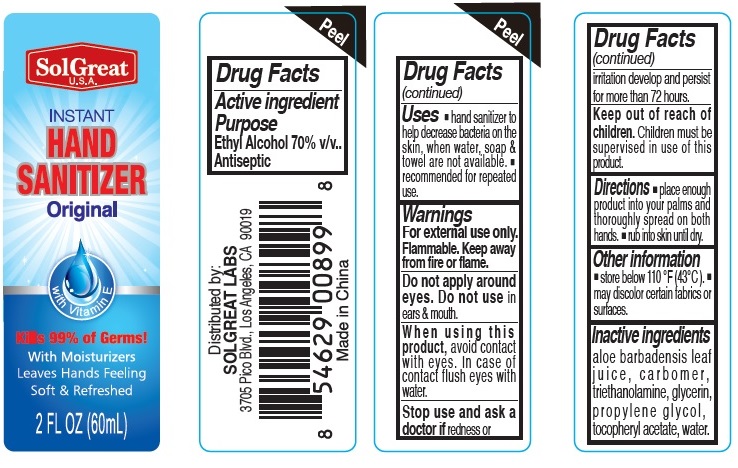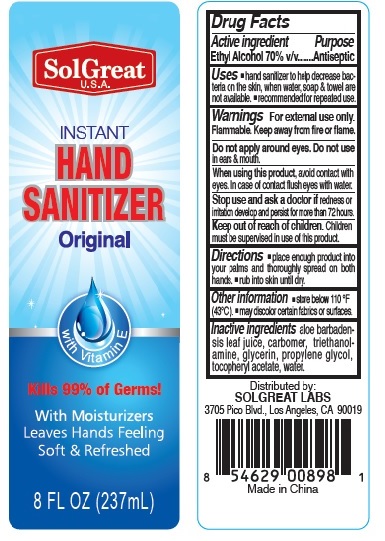 DRUG LABEL: SolGreat Instant Hand Sanitizer
NDC: 73913-001 | Form: GEL
Manufacturer: PANATURAL USA, INC.
Category: otc | Type: HUMAN OTC DRUG LABEL
Date: 20200422

ACTIVE INGREDIENTS: ALCOHOL 0.7 mL/1 mL
INACTIVE INGREDIENTS: ALOE VERA LEAF; WATER; CARBOMER 1342; TROLAMINE; GLYCERIN; PROPYLENE GLYCOL; .ALPHA.-TOCOPHEROL ACETATE

SolGreat Instant Hand Sanitizer

Active lngredient

Ethyl Alcohol

Purpose

Antiseptic

Uses

• hand sanitizer to help decrease bacteria on the skin, when water, soap & towel are not available.
• recommended for repeated use

Warnings

For external use only.

Flammable. Keep away from fire or flame.

Do not apply around eyes. Do not use in ears & mouth.

When using this product, avoid contact with eyes. In case of contact flush eyes with water.

Stop use and ask a doctor if redness or irritation develop and persist for more than 72 hours.

Directions

- place enough product into your palms and thoroughly spread on both hands.
- rub into skin until dry.

Inactives

aloe barbadensis leaf juice, carbomer, triethanolamine, glycerin, propylene glycol, tocopheryl acetate, water.

Keep out of reach of children.

Children must be supervised in use of this product.

Other information

- store below 110^0F (43oC).
- may discolor certain fabrics or surfaces.